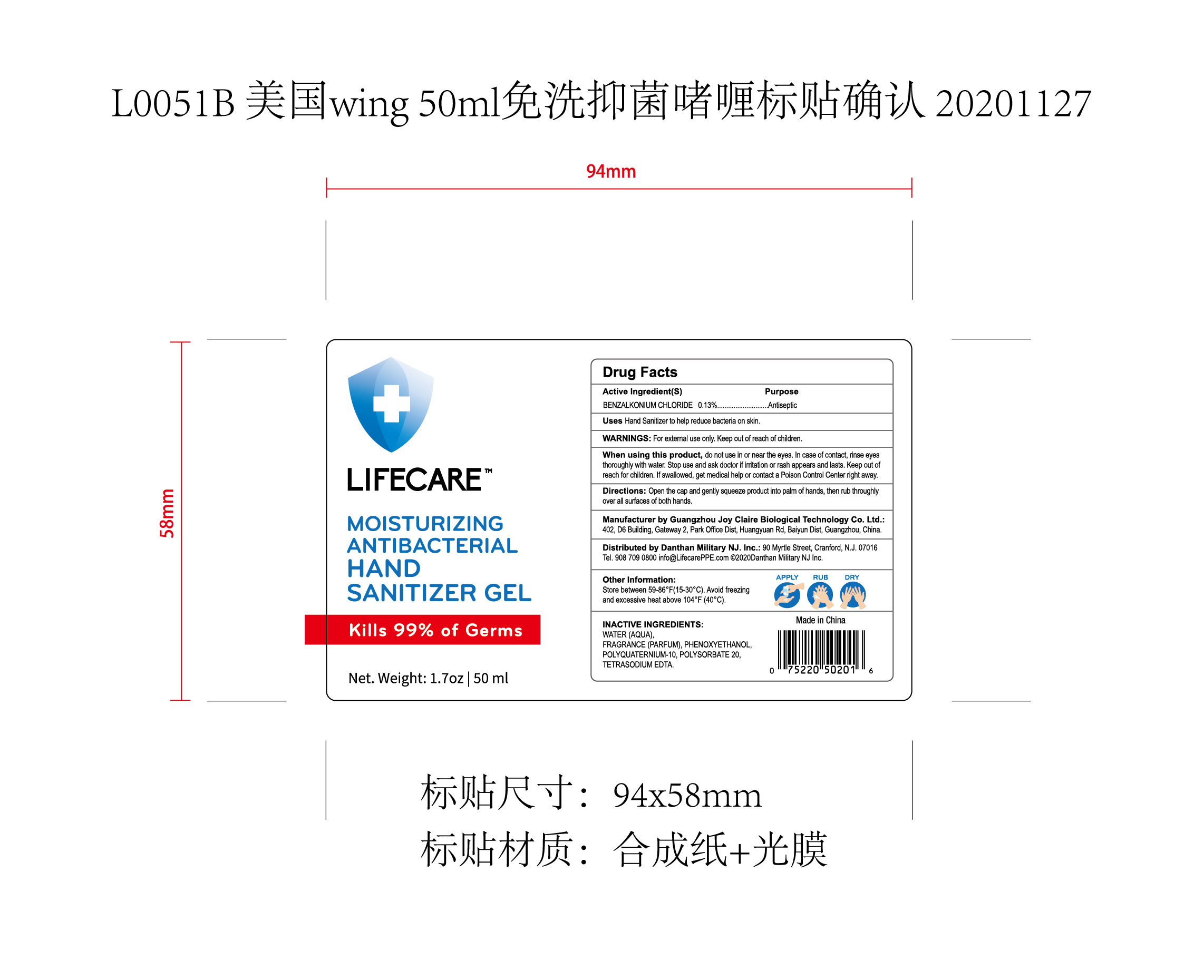 DRUG LABEL: MOISTURIZING ANTIBACTERIAL HAND SANITIZER
NDC: 74743-017 | Form: GEL
Manufacturer: Guangzhou Joy Claire Biological Technology Co.,Ltd
Category: otc | Type: HUMAN OTC DRUG LABEL
Date: 20201203

ACTIVE INGREDIENTS: BENZALKONIUM CHLORIDE 0.13 g/100 mL
INACTIVE INGREDIENTS: POLYSORBATE 20; EDETATE SODIUM; POLYQUATERNIUM-10 (1000 MPA.S AT 2%); FRAGRANCE LAVENDER & CHIA F-153480; PHENOXYETHANOL; WATER

74743-017
MOISTURIZING ANTIBACTERIAL HAND SANITIZER GEL

Active Ingredient(s)

BENZALKONIUM CHLORIDE 0.13%

Purpose

Antiseptic

Use

Hand Sanitizer to help reduce bacteria on skin

Warnings

For external use only, Keep out of reach of children.

do not use in or near the eyes. In case of contaot, rinse eyes thoroughly with water.

When using this product,
do not use in or near the eyes. In case of contaot, rinse eyes thoroughly with water.
Stop use and ask doctor if imtation or rash appears and lasts.
Keep out of reach for children. If swallowed, get medical help or contact a Poison Control Center right away.

Stop use and ask doctor if imtation or rash appears and lasts.

KEEP OUT OF REACH OF CHILDREN

Keep out of reach for children. If swallowed, get medical help or contact a Poison Control Center right away.

Directions

Open the cap and gently squeeze product into palm of hands, then rub throughly over all surfaces of both hands.

Other information

Store between 59-86F(15-30C). Avoid freezing and excessive heat above 104F (40C).

Inactive ingredients

WATER (AQUA).
FRAGRANCE (PARFUM), PHENOXYETHANOL,
POLYQUATERNIUM-10, POLYSORBATE 20,
TETRASODIUM EDTA.